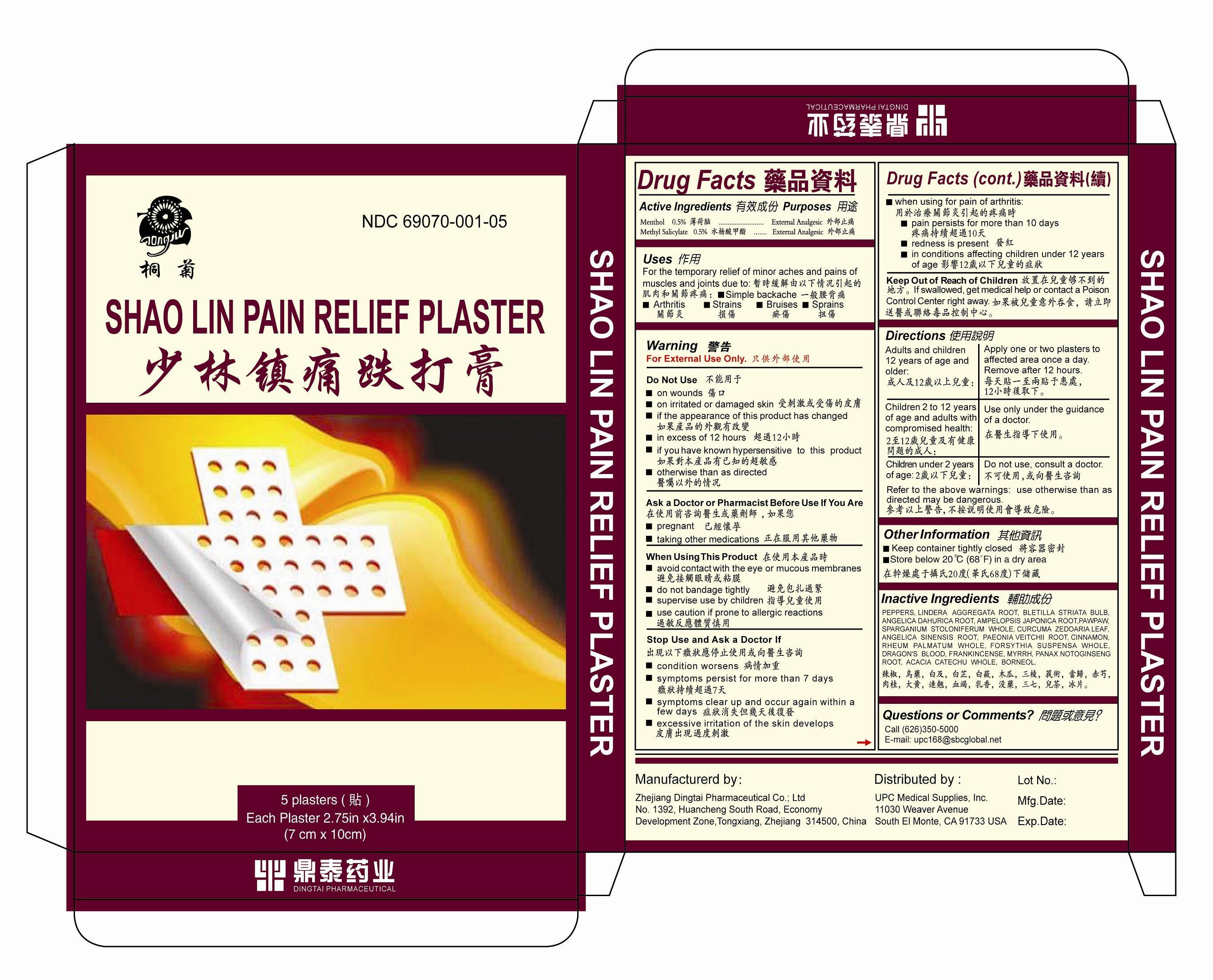 DRUG LABEL: Shao Lin Pain Relief Plaster
NDC: 69070-001 | Form: PLASTER
Manufacturer: Zhejiang Dingtai Pharmaceutical Co.; Ltd
Category: otc | Type: HUMAN OTC DRUG LABEL
Date: 20211019

ACTIVE INGREDIENTS: MENTHOL 0.5 g/100 g; METHYL SALICYLATE 0.5 g/100 g
INACTIVE INGREDIENTS: PEPPERS; LINDERA AGGREGATA ROOT; BLETILLA STRIATA BULB; ANGELICA DAHURICA ROOT; AMPELOPSIS JAPONICA ROOT; PAWPAW; SPARGANIUM STOLONIFERUM WHOLE; CURCUMA ZEDOARIA LEAF; ANGELICA SINENSIS ROOT; PAEONIA VEITCHII ROOT; CINNAMON; RHEUM PALMATUM WHOLE; FORSYTHIA SUSPENSA WHOLE; DRAGON'S BLOOD; FRANKINCENSE; MYRRH; PANAX NOTOGINSENG ROOT; ACACIA CATECHU WHOLE; BORNEOL

Zhejiang Dingtai Pharmaceutical Co.; Ltd

Active Ingredients

Menthol 0.5%

Methyl Salicylate 0.5%

Purpose

Menthol External Analgesic

Methyl Salicylate External Analgesic

Uses

For the temporary relief of minor aches and pains of muscles and joints due to:

simple backache

arthritis

strains

bruises

sprains

Warning

For External Use Only.

Do Not Use

on wounds

on irritated or damaged skin

if the appearance of this product has changed

in excess of 12 hours

if you have known hypersensitive to this product

otherwise than as directed

Ask a Doctor or Pharmacist Before Use If You Are

pregnant

taking other medications

When Using This Product

avoid contact with the eye or mucous membranes

do not bandage tightly

supervise use by children

use caution if prone to allergic reactions

Stop Use and Ask a Doctor If

condition worsens

symptoms persist for more than 7 days

symptoms clear up and occur again within a few days

excessive irritation of the skin develops

when using for pain of arthritis

pain persists for more than 10 days

redness is present

in conditions affecting children under 12 years of age

Keep Out of Reach of Children.

If swallowed, get medical help or contact a Poison Control Center right away.

Directions

Adults and children 12 years of age and older: Apply one or two plasters to affected area once a day. Remove after 12 hours.
Children 2 to 12 years of age and adults with compromised health: Use only under the guidance of a doctor.
Children under 2 years of age: Do not use, consult a doctor.
Refer to the above warnings: use otherwise than as directed may be dangerous.

Other Information

Keep container tightly closed.

Store below 20 ℃ (68 ℉) in a dry area.

Inactive Ingredients

PEPPERS, LINDERA AGGREGATA ROOT, BLETILLA STRIATA BULB, ANGELICA DAHURICA ROOT, AMPELOPSIS JAPONICA ROOT, PAWPAW, SPARGANIUM STOLONIFERUM WHOLE, CURCUMA ZEDOARIA LEAF, ANGELICA SINENSIS ROOT, PAEONIA VEITCHII ROOT, CINNAMON, RHEUM PALMATUM WHOLE, FORSYTHIA SUSPENSA WHOLE, DRAGON'S BLOOD, FRANKINCENSE, MYRRH, PANAX NOTOGINSENG ROOT, ACACIA CATECHU WHOLE, BORNEOL

Questions or Comments?

Call (626)350-5000 or

E-mail: upc168@sbcglobal.net

Manufacturerd by

Zhejiang Dingtai Pharmaceutical Co.; Ltd

No. 1392, Huancheng South Road, Economy Development Zone,

Tongxiang, Zhejiang 314500, China

Distributed by

UPC Medical Supplies, Inc.

11030 Weaver Avenue

South El Monte, CA 91733 USA